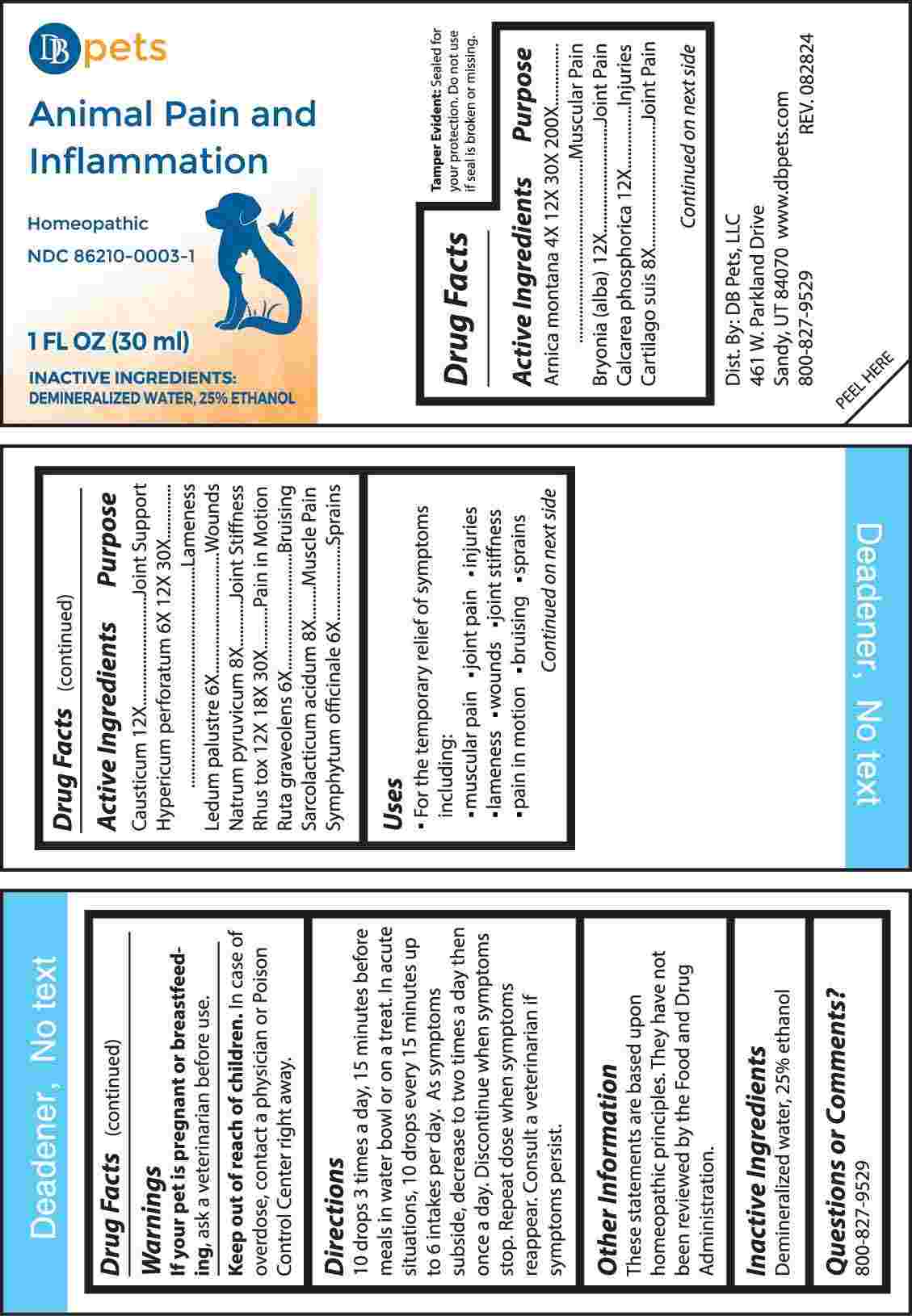 DRUG LABEL: Animal Pain and Inflammation
NDC: 86210-0003 | Form: LIQUID
Manufacturer: DB Pets LLC
Category: homeopathic | Type: OTC ANIMAL DRUG LABEL
Date: 20250114

ACTIVE INGREDIENTS: ARNICA MONTANA WHOLE 4 [hp_X]/1 mL; BRYONIA ALBA ROOT 12 [hp_X]/1 mL; TRIBASIC CALCIUM PHOSPHATE 12 [hp_X]/1 mL; SUS SCROFA CARTILAGE 8 [hp_X]/1 mL; CAUSTICUM 12 [hp_X]/1 mL; HYPERICUM PERFORATUM WHOLE 6 [hp_X]/1 mL; RHODODENDRON TOMENTOSUM LEAFY TWIG 6 [hp_X]/1 mL; SODIUM PYRUVATE 8 [hp_X]/1 mL; TOXICODENDRON PUBESCENS LEAF 12 [hp_X]/1 mL; RUTA GRAVEOLENS FLOWERING TOP 6 [hp_X]/1 mL; LACTIC ACID, L- 8 [hp_X]/1 mL; COMFREY ROOT 6 [hp_X]/1 mL
INACTIVE INGREDIENTS: WATER; ALCOHOL

DRUG FACTS:

ACTIVE INGREDIENTS:

Arnica Montana 4X, 12X, 30X, 200X, Bryonia (Alba) 12X, Calcarea Phosphorica 12X, Cartilago Suis 8X, Causticum 12X, Hypericum Perforatum 6X, 12X, 3OX, , Ledum Palustre 6X, Natrum Pyruvicum 8X, Rhus Tox 12X, 18X, 30X, Ruta Graveolens 6X, Sarcolacticum Acidum 8X, Symphytum Officinale 6X.

PURPOSE:

Arnica Montana – Muscular Pain, Bryonia (Alba) – Joint Pain, Calcarea Phosphorica - Injuries, Cartilago Suis – Joint Pain, Causticum – Joint Support, Hypericum Perforatum - Lameness, Ledum Palustre - Wounds, Natrum Pyruvicum – Joint Stiffness, Rhus Tox – Pain in Motion, Ruta Graveolens - Bruising, Sarcolacticum Acidum – Muscle Pain, Symphytum Officinale - Sprains

USES:

• For the temporary relief of symptoms including:

•muscular pain •joint pain •injuries •lameness

•wounds •joint stiffness •pain in motion •bruising •sprains

These statements are based upon homeopathic principles. They have not been reviewed by the Food and Drug Administration.

WARNINGS:

If your pet is pregnant or breastfeeding, ask a veterinarian before use.

Keep out of reach of children. In case of overdose, contact a physician or Poison Control Center right away.

Tamper Evident: Sealed for your protection. Do not use if seal is broken or missing.

KEEP OUT OF THE REACH OF CHILDREN:

In case of overdose, contact a physician or Poison Control Center right away.

DIRECTIONS:

10 drops 3 times a day, 15 minutes before meals in water bowl or on a treat. In acute situations, 10 drops every 15 minutes up to 6 intakes per day. As symptoms subside, decrease to two times a day then once a day. Discontinue when symptoms stop. Repeat dose when symptoms reappear. Consult a veterinarian if symptoms persist.

INACTIVE INGREDIENTS:

Demineralized water, 25% ethanol

QUESTIONS:

Dist. By: DB Pets, LLC

461 W. Parkland Drive

Sandy, UT 84070

www.dbpets.com

800-827-9529

PACKAGE LABEL DISPLAY:

DB pets

Animal Pain and

Inflammation

Homeopathic

NDC 86210-0003-1

1 FL OZ (30 ml)